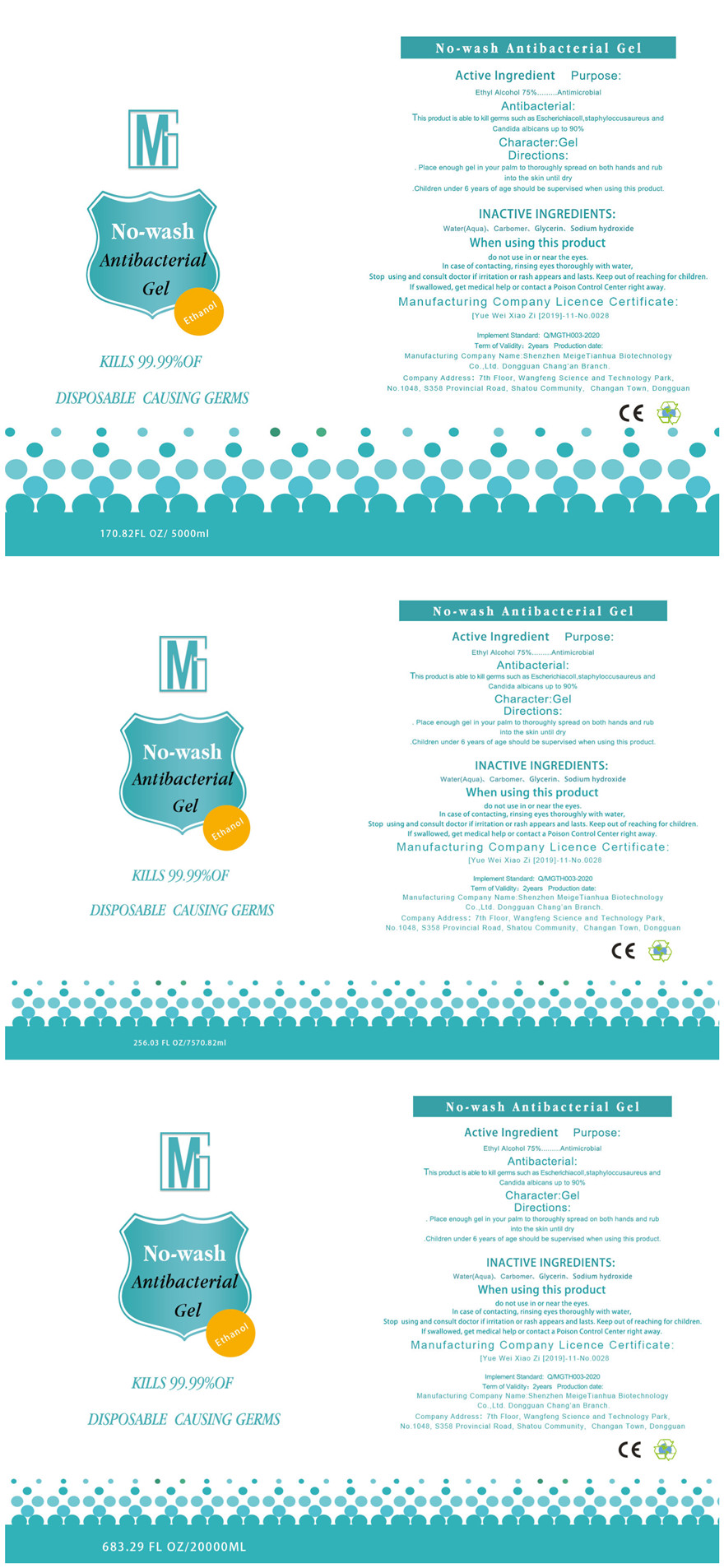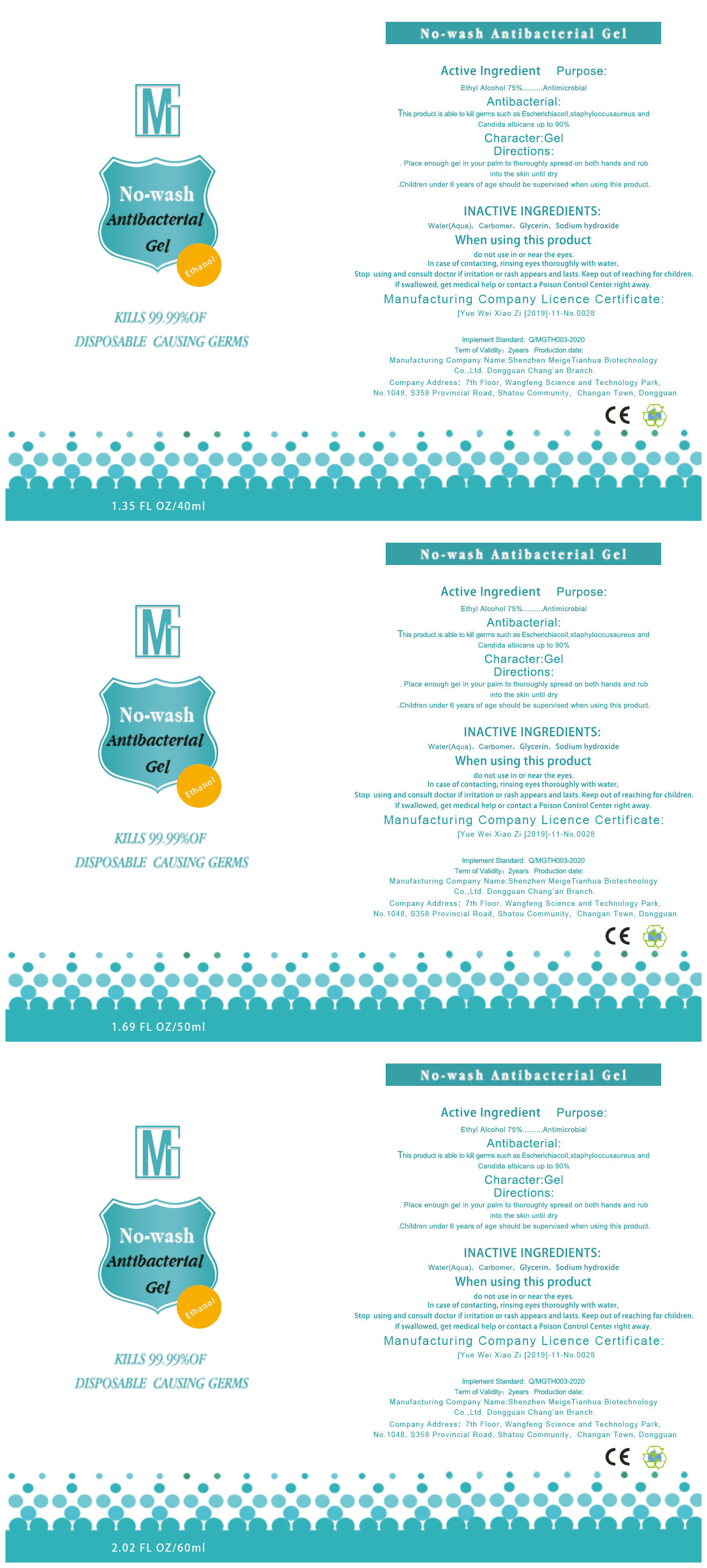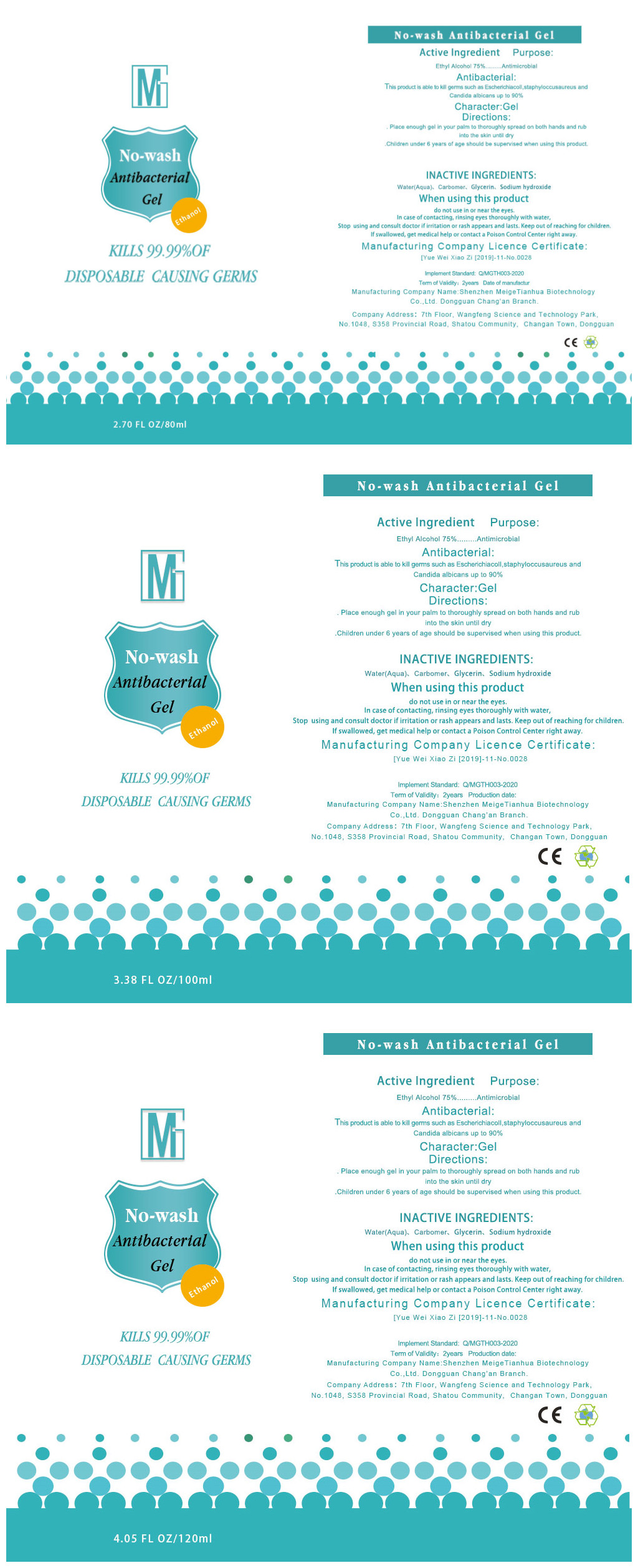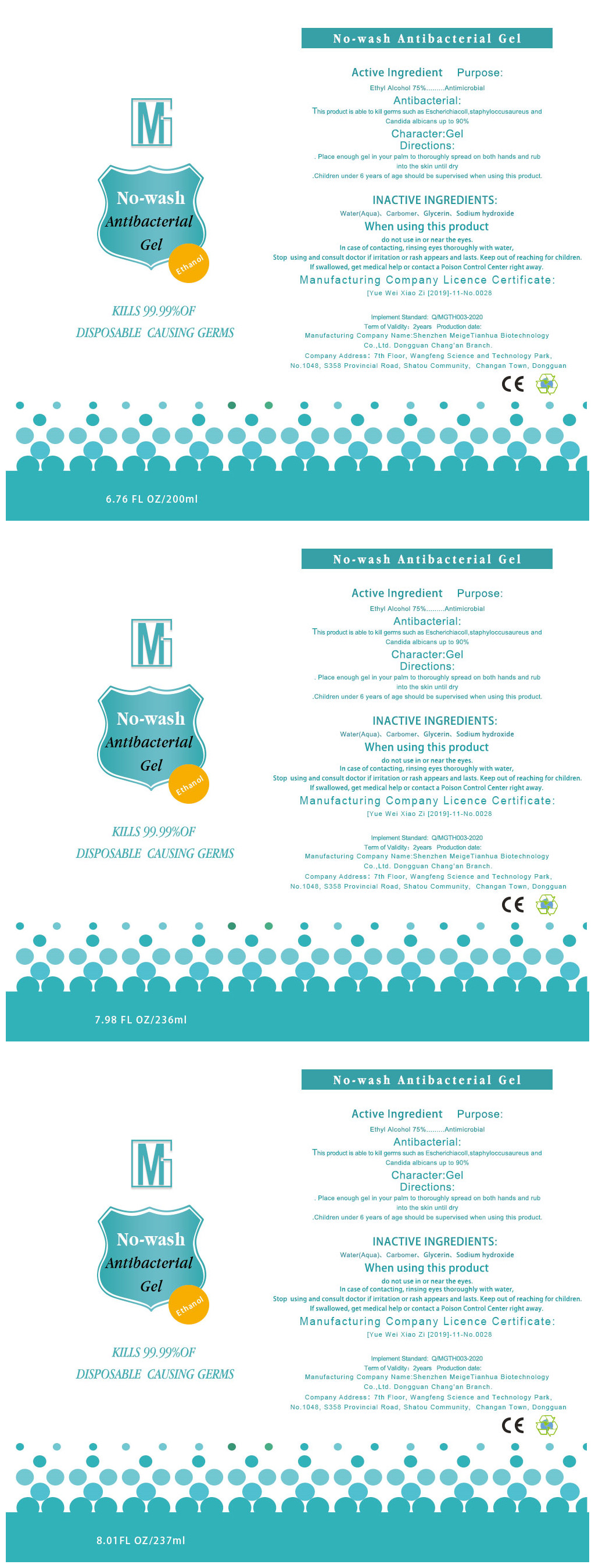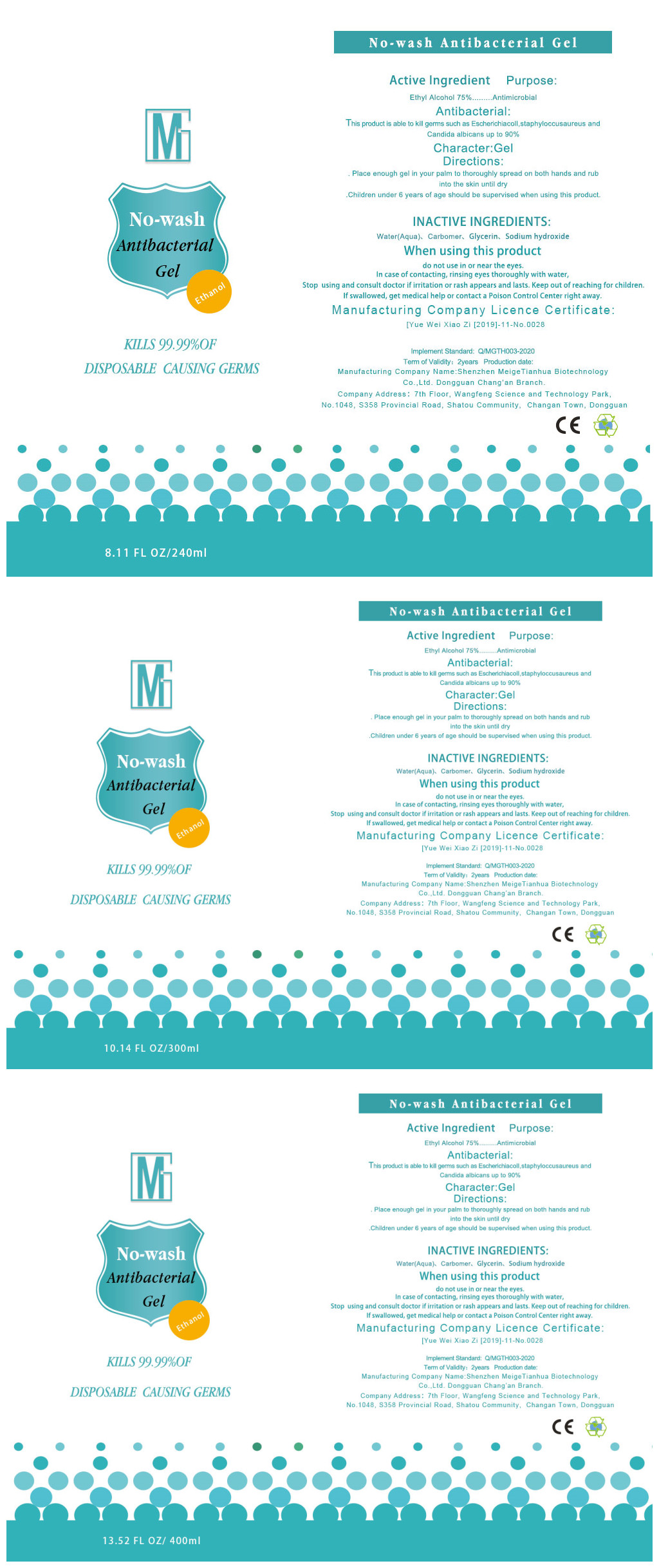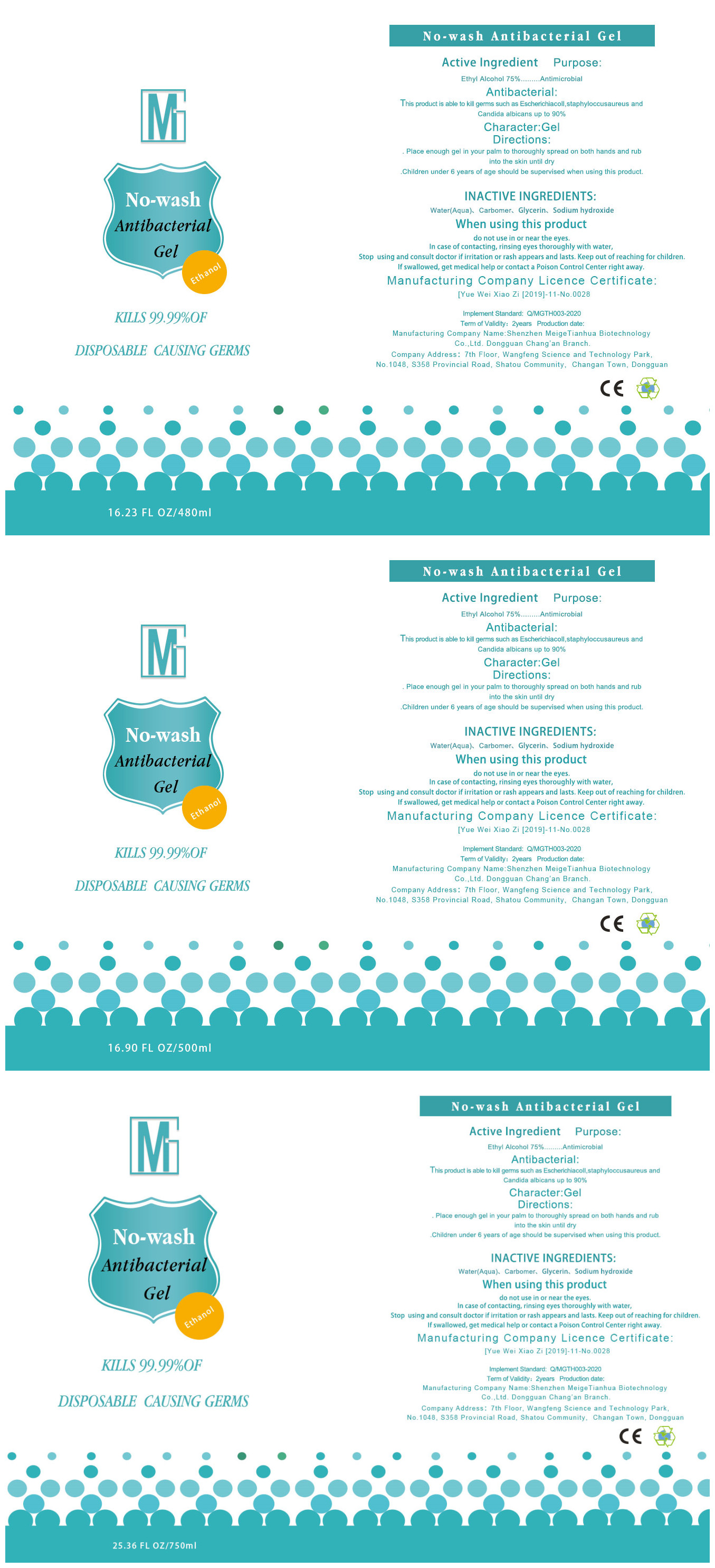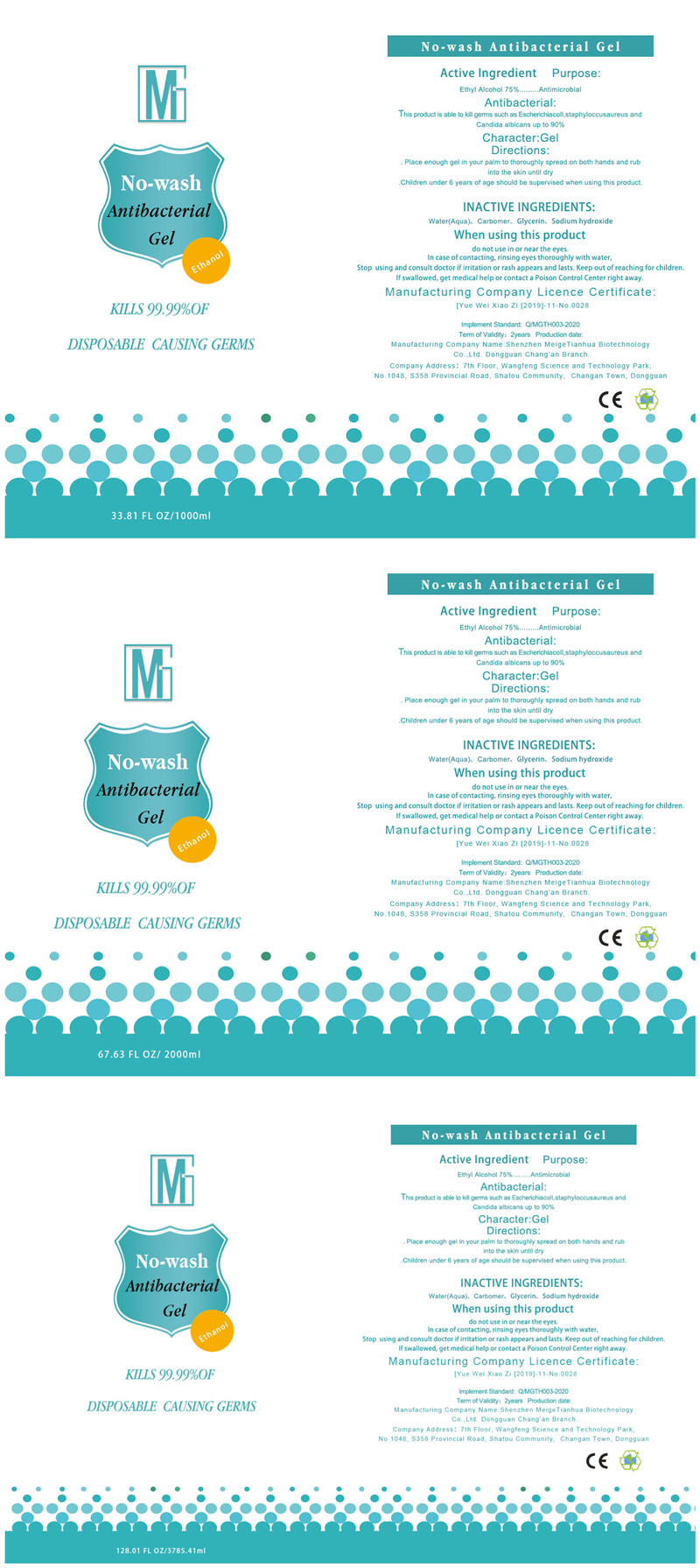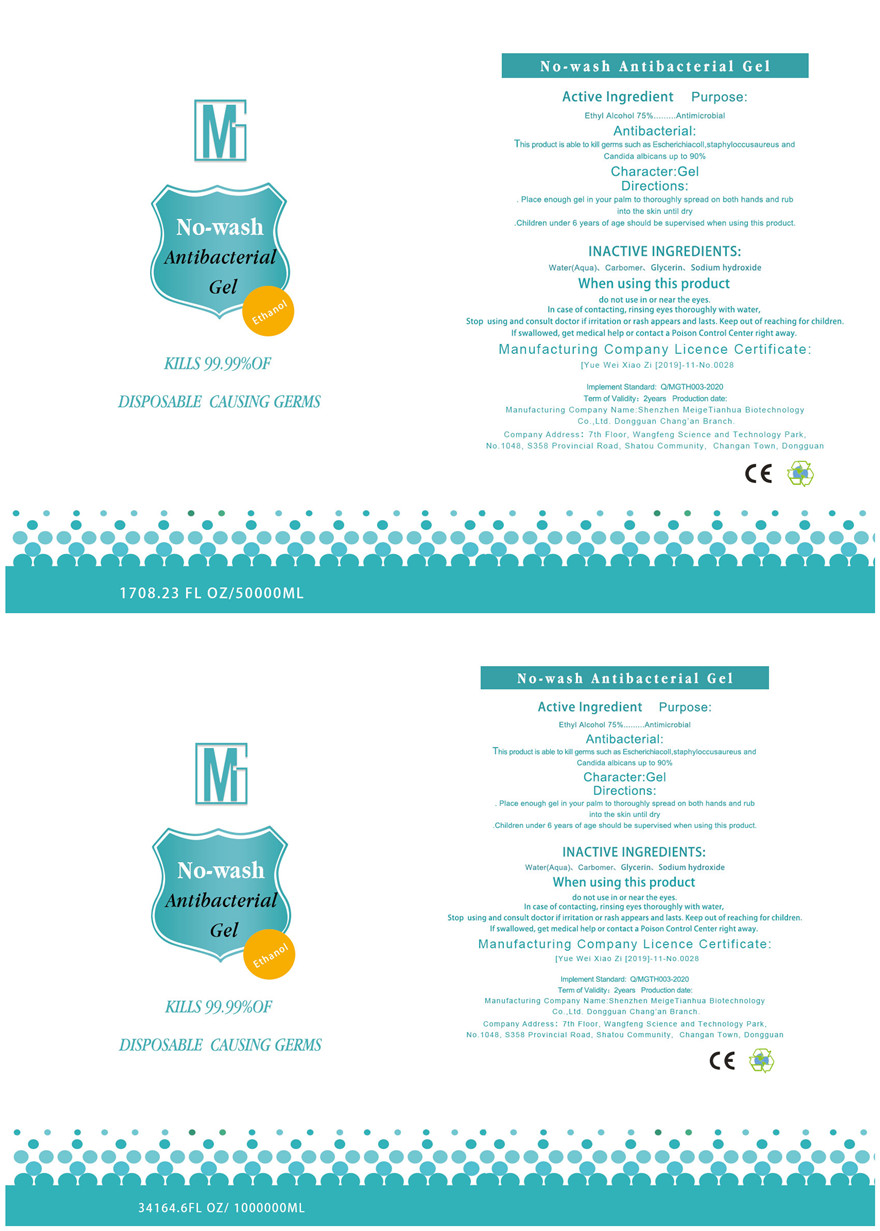 DRUG LABEL: No-wash Antibacterial Gel
NDC: 74272-013 | Form: GEL
Manufacturer: Shenzhen Meige Tianhua Biological Technology Co., Ltd. Dongguan Changan Branch
Category: otc | Type: HUMAN OTC DRUG LABEL
Date: 20200623

ACTIVE INGREDIENTS: ALCOHOL 75 mL/100 mL
INACTIVE INGREDIENTS: GLYCERIN; SODIUM HYDROXIDE; CARBOMER HOMOPOLYMER, UNSPECIFIED TYPE; WATER

No-wash Antibacterial Gel

Active Ingredient

Ethyl Alcohol 75%

Purpose

Antimicrobial

When using this product

do not use in or near the eyes.In case of contacting, rinsing eyes thoroughly with water,

Stop using and consult doctor if irritation or rash appears and lasts.Keep out of reaching for children.

If swallowed,get medical help or contact a Poison Control Center right away.

Directions

Place enough gel in your palm to thoroughly spread on both hands and rub into the skin until dry

Children under 6 years of age should be supervised when using this product.

INACTIVE INGREDIENTS

Water(Aqua) 、Carbomer、Glycerin、Sodium hydroxide